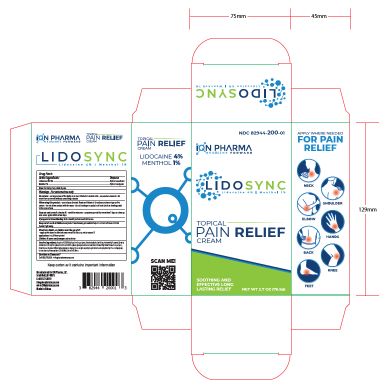 DRUG LABEL: LidoSync
NDC: 82944-200 | Form: CREAM
Manufacturer: iON Pharma, LLC
Category: otc | Type: HUMAN OTC DRUG LABEL
Date: 20240819

ACTIVE INGREDIENTS: LIDOCAINE HYDROCHLORIDE ANHYDROUS 3.1 g/76.5 g; LEVOMENTHOL 0.8 g/76.5 g
INACTIVE INGREDIENTS: PHENOXYETHANOL; GLYCERYL 1-STEARATE; ETHYLHEXYLGLYCERIN; STEARETH-21; HYDROXYETHYL ACRYLATE/SODIUM ACRYLOYLDIMETHYL TAURATE COPOLYMER (45000 MPA.S AT 1%); DIHEXADECYL PHOSPHATE; AMINOMETHYLPROPANOL; DIMETHICONE 350; CETETH-10 PHOSPHATE; DIMETHICONE/VINYL DIMETHICONE CROSSPOLYMER (SOFT PARTICLE); ACRYLATES/C10-30 ALKYL ACRYLATE CROSSPOLYMER (60000 MPA.S); ALCOHOL 95%; WATER; CYCLOMETHICONE 5; CETOSTEARYL ALCOHOL; ALOE VERA LEAF; ISOHEXADECANE; EDETATE DISODIUM ANHYDROUS

Lidosync Cream (Lidocaine 4%, Menthol 1%)

LidoSync Drug Facts Active Ingredients

Active ingredients: Purpose:

Lidocaine HCl 4%...................................Topical Anesthetic

Menthol 1%.............................................Topical Analgesic

Uses

Uses: For Temporary relief of pain.

LidoSync Warnings Do Not Use

Do not use on large areas of the body or on cut, irritated or swollen skin on puncture wounds for more than one week without consulting a doctor

LidoSync When using section

When using this product use only as directed. Read and follow all directions and warnings on this carton. do not allow contact with the eyes • do not bandage or apply local heat (such as heating pads) to the area of use

LidoSync Stop use and consult doctor if section

Stop use and consult a doctor if condition worsens symptoms persist for more than 7 days or clear up and occur again within a few days

LidoSync If pregnant or breastfeeding section

If pregnant or breastfeeding: Ask a health professional before use.

Lidosync keep out of reach of children and pets section

Keep out of reach of children and pets. If swallowed, get medical help or contact a Poison Control
Center right away.

Directions:

Adults, or children over the age of 12: apply a thin layer to affected area every 6 to 8 hours, not to exceed 3 applications in a 24 hour period
Children 12 years and younger: ask a doctor

Inactive Ingredients

Inactive ingredients: Acrylates/C10-30 Alkyl Acrylate Crosspolymer, Aloe barbadensis Leaf Juice, Aminomethyl Propanol, Cetearyl
Alcohol (and) Dicetyl Phosphate (and) Ceteth-10 Phosphate, Cyclopentasiloxane (and) Dimethicone/Vinyl Dimethicone Crosspolymer,
Dimethicone, Disodium EDTA, Ethylhexylglycerin, Glyceryl stearate, Hydroxyethyl Acrylate/Sodium Acryloyldimethyl Taurate Copolymer, Isohexadecane, Phenoxyethanol, SD Alcohol, Steareth-21, Water.

Questions or comments section

Questions or Comments?
Call 833.711.8833 • info@ionpharmausa.com